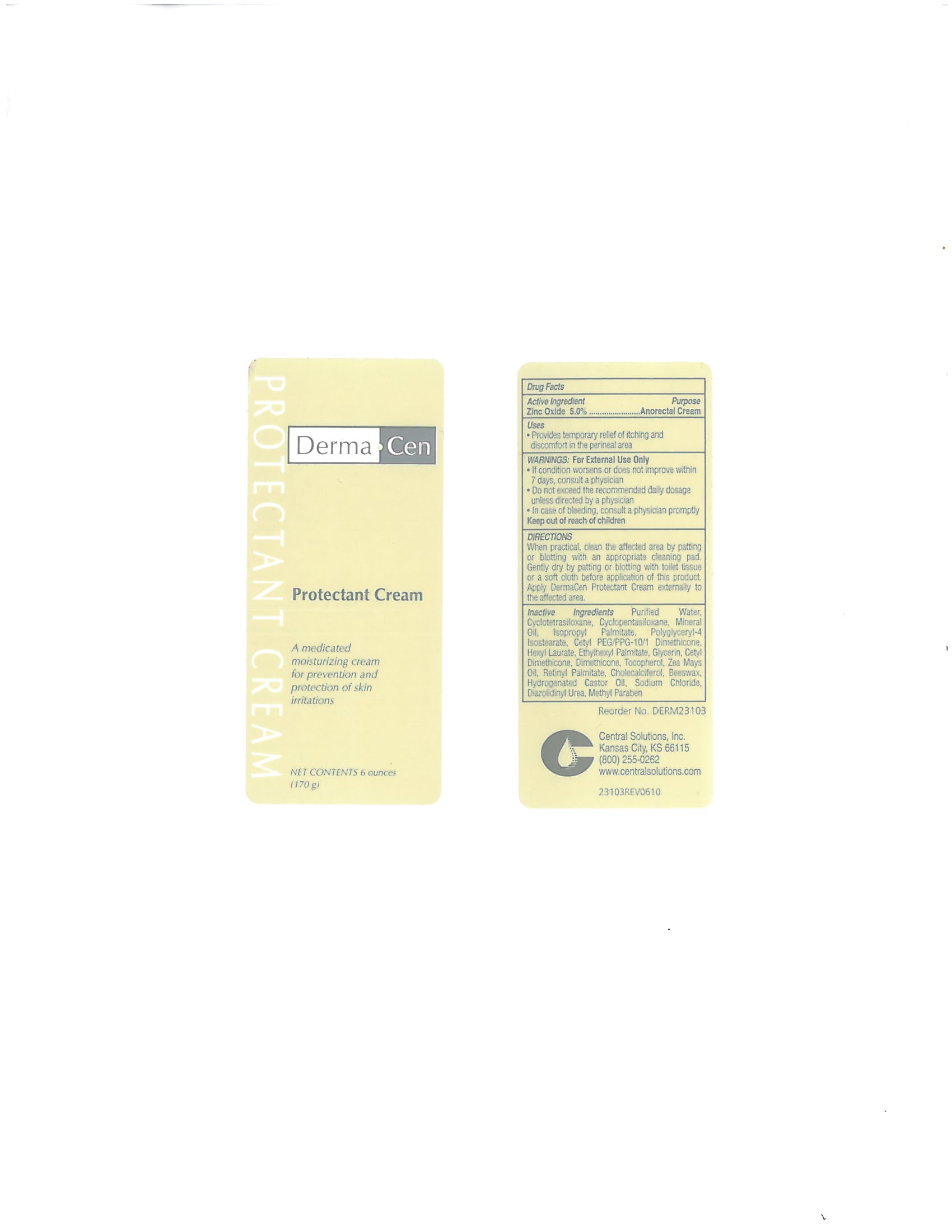 DRUG LABEL: DermaCen Protectant
NDC: 62654-313 | Form: CREAM
Manufacturer: Central Solutions Inc
Category: otc | Type: HUMAN OTC DRUG LABEL
Date: 20181206

ACTIVE INGREDIENTS: ZINC OXIDE 5.0 g/100 g
INACTIVE INGREDIENTS: QUADROSILAN; CYCLOMETHICONE 5; MINERAL OIL; ISOPROPYL PALMITATE; POLYGLYCERYL-4 ISOSTEARATE; HEXYL LAURATE; ETHYLHEXYL PALMITATE; GLYCERIN; DIMETHICONE; TOCOPHEROL; CORN OIL; VITAMIN A PALMITATE; CHOLECALCIFEROL; YELLOW WAX; HYDROGENATED CASTOR OIL; SODIUM CHLORIDE; DIAZOLIDINYL UREA; METHYLPARABEN; WATER

Drug Facts

Active Ingredient

Zinc oxide 5.0%

Purpose

Anorectal Cream

Uses

Provides temporary relief of itching and discomfort in the perineal area

Warnings

For External Use Only

If condition worsens or does not improve within 7 days, consult a physician

Do not exceed the recommended daily dosage unless directed by a physician

In case of bleeding, consult a physician promptly

Keep out of reach of children

Directions

When practical, clean the affected area by patting or blotting with an appropriate cleaning pad. Gently dry by patting or blotting with toilet tissue or a soft cloth before application of this product. Apply DermaCen Protectant Cream externally to the affected area.

Inactive Ingredients

Purified Water, Cyclotetrasiloxane, Cyclopentasiloxane, Mineral Oil, Isopropyl Palmitate, Polyglyceryl-4 Isostearate, Cetyl PEG/PPG-10/1 Dimethicone, Hexyl Laurate, Ethylhexyl Palmitate, Glycerin, Cetyl Dimethicone, Dimethicone, Tocopherol, Zea Mays Oil, Retinyl Palmitate, Cholecalciferol, Beeswax, Hydrogenated Castor Oil, Sodium Chloride, Diazolidinyl Urea, Methyl Paraben

PACKAGE LABEL

DermaCen

Protectant Cream

A medicated

moisturizing cream

for prevention and

protection of skin

irritations

Net Contents 6 ounces (170g)